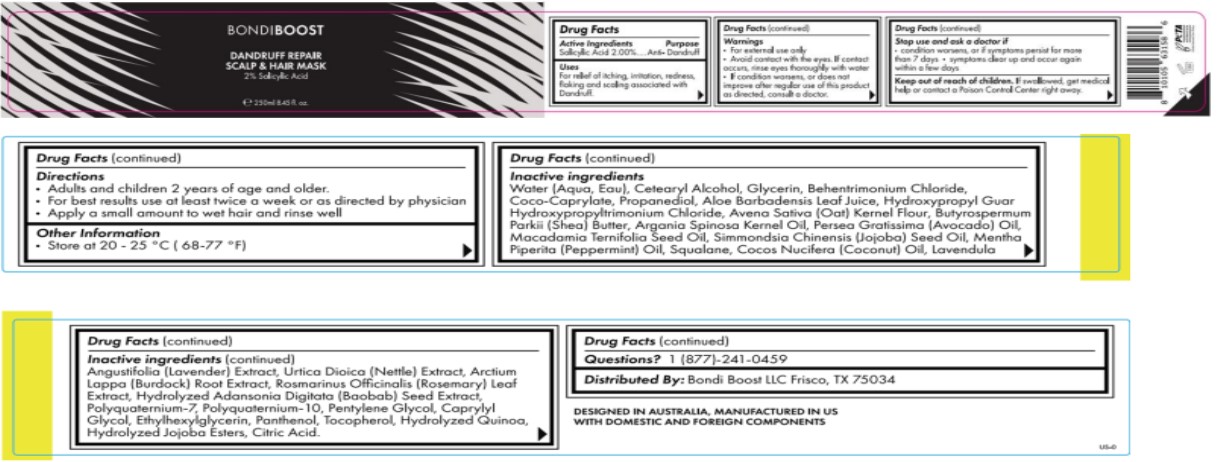 DRUG LABEL: Dandruff Repair Mask
NDC: 84169-003 | Form: CREAM
Manufacturer: Bondi Boost U.S LLC
Category: otc | Type: HUMAN OTC DRUG LABEL
Date: 20241223

ACTIVE INGREDIENTS: SALICYLIC ACID 20 mg/1 mL
INACTIVE INGREDIENTS: ETHYLHEXYLGLYCERIN; ALOE VERA LEAF; LAVANDULA ANGUSTIFOLIA FLOWERING TOP; URTICA DIOICA LEAF; PROPANEDIOL; ADANSONIA DIGITATA SEED; JOJOBA OIL; COCO-CAPRYLATE; WATER; ARCTIUM LAPPA ROOT; ROSEMARY; CITRIC ACID MONOHYDRATE; PENTYLENE GLYCOL; ARGAN OIL; OATMEAL; COCONUT OIL; POLYQUATERNIUM-10 (400 CPS AT 2%); HYDROXYPROPYL GUAR HYDROXYPROPYLTRIMONIUM CHLORIDE; AVOCADO OIL; MACADAMIA OIL; POLYQUATERNIUM-7 (70/30 ACRYLAMIDE/DADMAC; 900 KD); SQUALENE; SHEA BUTTER; PANTHENOL; CHENOPODIUM QUINOA WHOLE; PEPPERMINT OIL; HYDROLYZED JOJOBA ESTERS (ACID FORM); TOCOPHEROL; BEHENTRIMONIUM CHLORIDE; CAPRYLYL GLYCOL; CETOSTEARYL ALCOHOL; GLYCERIN

Bondi Boost Dandruff Repair Mask

Active Ingredients | Purpose
Salicylic Acid 2.00% | Anti- Dandruff

Stop use and ask a doctor if

- condition worsens, or if symptoms persist for more than 7 days
- symptoms clear up and occur again within a few days

Keep out of reach of children.

If swallowed, get medical help or control a Poison Control Center right away.

PURPOSE

Anti Dandruff

Warnings

- For External use only
- Avoid Contact with the eyes. If contact occurs, rinse eyes thoroughly with ware
- If condition worsens, or does not improve after regular use of this product as directed, consult a doctor.

Stop use and ask a doctor if

- condition worsens, or if symptoms persist for more than 7 days
- systoms clear up and occur again within a few days

Questions? 1(877)-241-0459

INACTIVE INGREDIENT

Water (Aqua, Eau), Ceterayl Alchol, Glycerin, Behentrimonium Chloride, Coco- Caprylate, Propanediol, Aloe Barbadensis Leaf Juice,

Hydroxypropyl Guar Hydroxypropyltrimonium Chloride, Avena Sativa (Oat) Kernel Flour, Butyrospermum Parkii (Shea) Butter, Argania Spinosa Kernal Oil, Persea Gratissima (Avocado) Oil, Macadamia Ternifolia Seed Oil, Simmondsia Chinensis (jojoba) Seed Oil, Mentha Piperita (Peppermint) Oil, Squalane, Cocos Nucifera (Coconut) Oil, Lavendula Angustifolia (Lavender) Extract, Urtica Dioica (Nettle) Extract, Arctium Lappa (Burdock) Root Extract, Rosmarinus Officinalis (Rosemary) Leaf Extract, Hydrolyzed Adansonia Digitata (Baobab) Seed Extract, Polyquaternium-7, Polyquaternium-10, Pentylene Glycol, Caprylyl Glycol, Ethylhexylglycerin, Panthenol, Tocopherol, Hyrdrolyzed Quinoa, Hyrdolyzed Jojoba Estrs, Citic acid.

Uses:

For Relief of itching, irritation, redness, flaking and scaling associated with Dandruff.